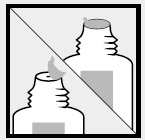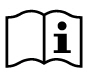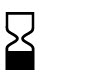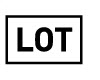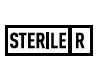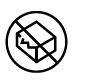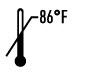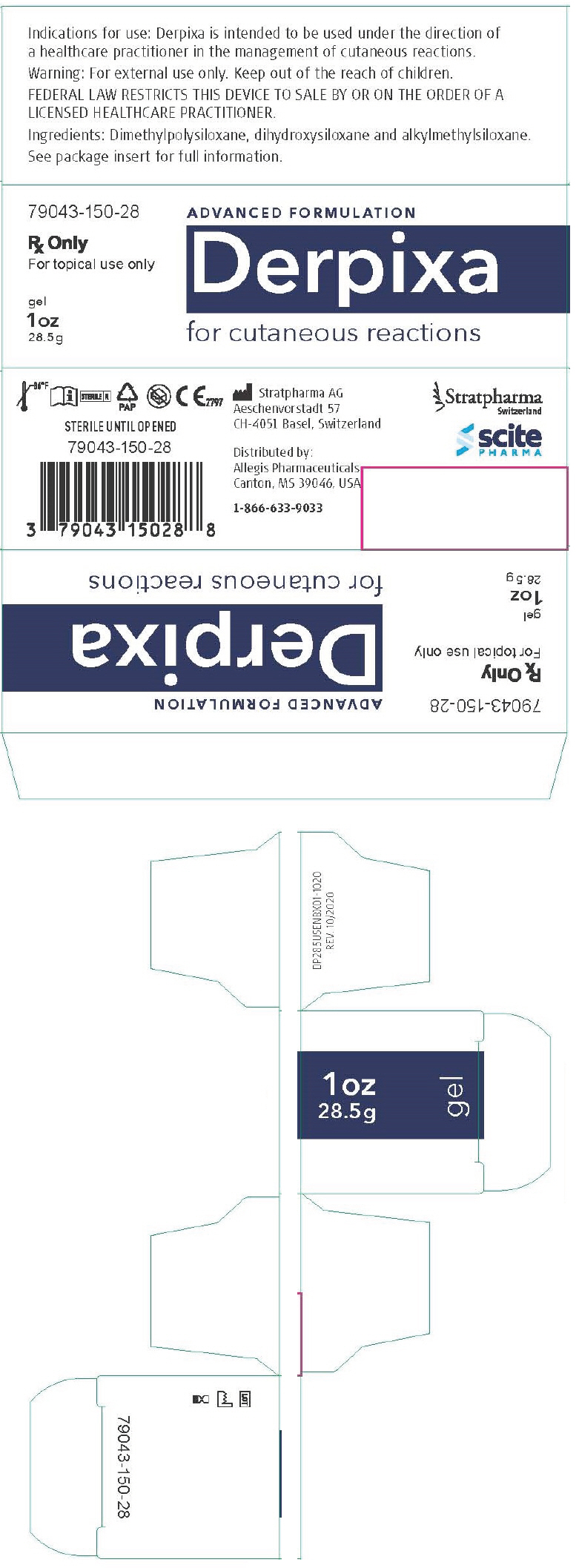 DRUG LABEL: Derpixa
NDC: 79043-150
Manufacturer: Scite Pharma, LLC
Category: other | Type: MEDICAL DEVICE
Date: 20230717
INACTIVE INGREDIENTS: DIMETHICONE; DIMETHICONOL (2000 CST); DIDECYLDIMONIUM CHLORIDE

ADVANCED FORMULATION
Derpixa
for cutaneous reactions

Rx Only

For topical use only

Federal Law restricts this device to sale by or on the order of a licensed healthcare practitioner.

Description

Derpixa is an occlusive, non-resorbable, self-drying and transparent gel.

When used as directed Derpixa dries to form a protective layer that is gas permeable and waterproof which hydrates and protects compromised skin areas and superficial wounds from chemical and microbial invasion.

Derpixa helps to promote a moist healing environment.

This moist wound healing environment promotes faster re-epithelialization [Losi P et al. J Mater Sci Mater Med.2012;23(9):2235–43] and reduces the skin's acute inflammatory response.

Derpixa is suitable for large surface areas and contoured skin like head, face, hand and foot, as well as joints and hairy areas without the need for shaving.

Indication for use

Derpixa is intended to be used under the direction of healthcare practitioners in the management of cutaneous reactions.

Derpixa is indicated for use on all types of wounds, toxic and compromised skin including:

- Cutaneous reactions
- Pruritic, itchy skin
- Xerotic, dry skin
- Desquamation
- Fissures of skin and nail folds
- Blisters
- Medical Adhesive-Related Skin Injuries (MARSI)
- Erythema
- Infusion reactions
- Rashes, including: Maculopapular rash, hand-foot syndrome, GVHD, acneiform reaction, peri – and appendageal (hair follicles, sweat glands)

Derpixa is indicated for the relief of dry, itching, flaking, peeling and irritated skin, as well as the symptomatic relief of pain, redness and heat sensation.

Derpixa may be directly applied to dry skin, open wounds and compromised or desquamating skin surfaces, including cutaneous rashes.

Derpixa gel is bacteriostatic and inert.

It contains no alcohols, parabens or fragrances.

Derpixa can be used with or without a secondary protective dressing.

Derpixa is suitable for children and people with sensitive skin.

Derpixa is intended for single patient use.

Directions for use

On the first use of 1 oz (28.5 g) tubes remove the cap, then the protective seal and close with the cap after use.

Ensure that the affected superficial area is clean and dry.

Apply a very thin layer of Derpixa directly to the affected area and allow the gel to dry.

When applied correctly to exposed areas, Derpixa should be dry in 5–6 minutes.

If it takes longer to dry you have probably applied too much.

Gently remove the excess with a clean tissue or gauze and allow the drying process to continue.

Once dry, Derpixa may be covered by sunscreen, cosmetics and clothing.

Derpixa should be applied at least twice daily to affected areas, as needed or as advised by your physician.

For best results Derpixa should be maintained in continuous contact with the skin (24 hours a day/7 days a week).

How much Derpixa do I need?

Derpixa gel is an advanced formulation that requires substantially less product per application than typical creams or gels.

Derpixa 1 oz (28.5 g) is enough to treat an area of 6 × 12 inch (15 × 30 cm) twice per day for 30 days.

Warning

- For external use only.
- Derpixa should not be placed in contact with the eyes.
- Derpixa should not be applied over topical medications unless advised by your physician.
- Derpixa may stain clothing if not completely dry. If staining occurs, dry cleaning should be able to remove it without damaging the fabric.
- For correct storage please reclose the tube tightly with the cap.
- If irritation occurs, discontinue use and consult your physician.
- Keep out of the reach of children.
- Do not use after the expiration (EXP) date printed on the tube. The expiration (EXP) date does not change once the tube has been opened.
- Do not use if the tube is damaged.

Contraindications

Do not administer to patients with known hypersensitivity to the ingredients of this product.

STERILE UNTIL OPENED

Ingredients: Dimethylpolysiloxane, dihydroxysiloxane and alkylmethylsiloxane.

How supplied

Derpixa 1 oz (28.5 g) tube

Product identification code: 79043-150-28

Consult instructions for use

Use by date

Batch code

Sterilized using irradiation

Do not use if the tube is damaged

Upper limit of temperature

Stratpharma AG
Aeschenvorstadt 57
CH-4051 Basel
Switzerland

Distributed by
Allegis Pharmaceuticals
Canton, MS 39046, USA

Date of preparation of this
information: 10/2020

Stratpharma
Switzerland

scite
PHARMA

Questions:
1-866-633-9033

CE

DP000USENPI01-1020

PRINCIPAL DISPLAY PANEL - 28.5 g Tube Box

79043-150-28

Rx Only
For topical use only

ADVANCED FORMULATION
Derpixa
for cutaneous reactions

gel
1 oz
28.5 g